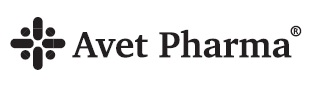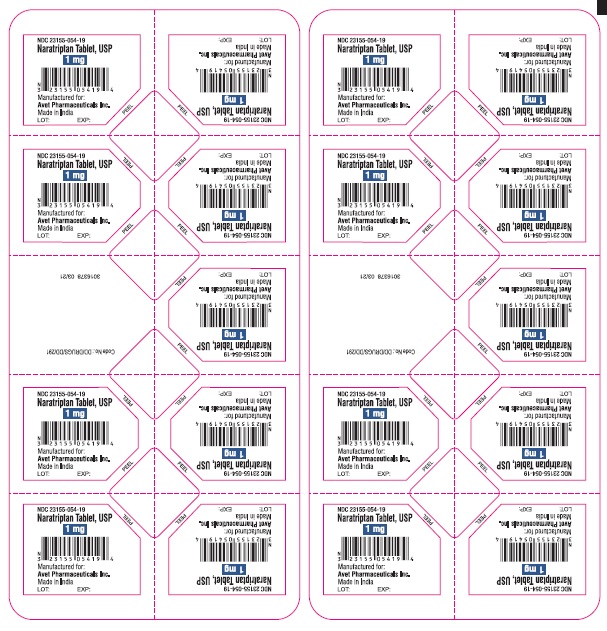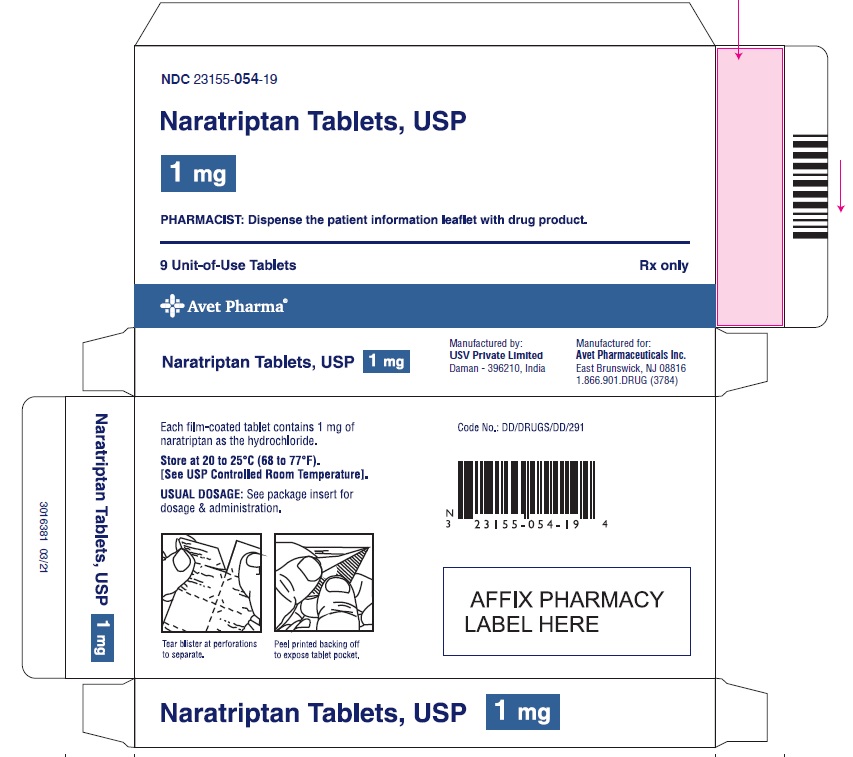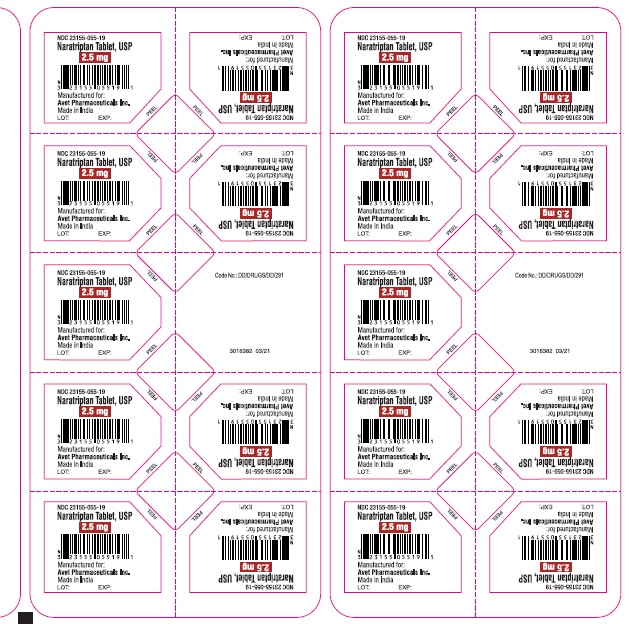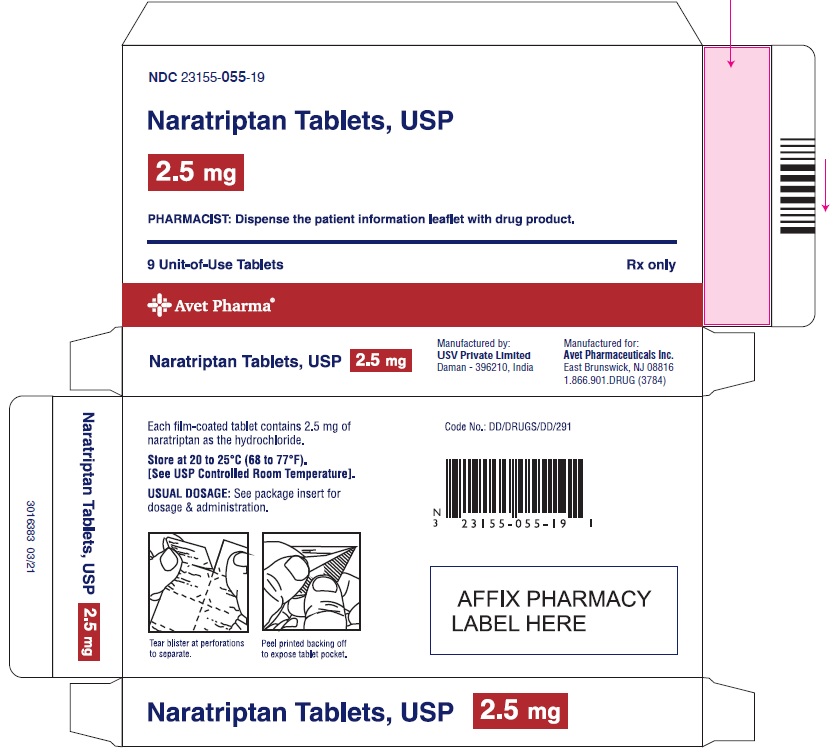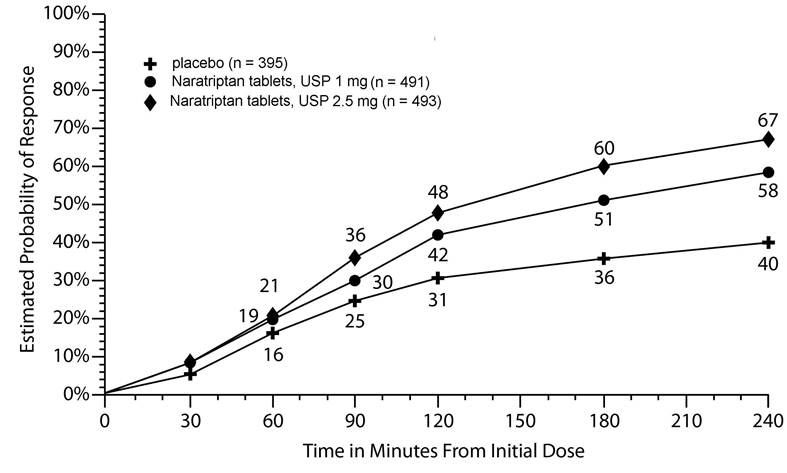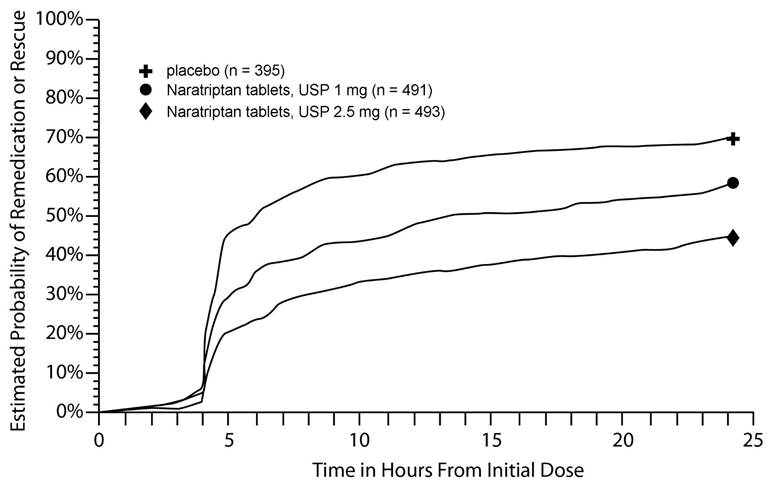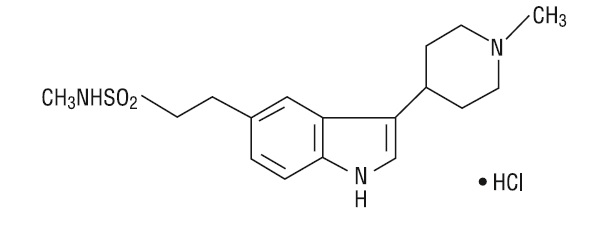 DRUG LABEL: naratriptan
NDC: 23155-054 | Form: TABLET
Manufacturer: Heritage Pharmaceuticals Inc. d/b/a Avet Pharmaceuticals Inc.
Category: prescription | Type: HUMAN PRESCRIPTION DRUG LABEL
Date: 20251030

ACTIVE INGREDIENTS: NARATRIPTAN HYDROCHLORIDE 1 mg/1 1
INACTIVE INGREDIENTS: ANHYDROUS LACTOSE; CELLULOSE, MICROCRYSTALLINE; CROSCARMELLOSE SODIUM; MAGNESIUM STEARATE; HYPROMELLOSE 2910 (5 MPA.S); TITANIUM DIOXIDE; POLYETHYLENE GLYCOL 400; FERRIC OXIDE YELLOW

HIGHLIGHTS OF PRESCRIBING INFORMATION

These highlights do not include all the information needed to use NARATRIPTAN TABLETS safely and effectively. See full prescribing information for NARATRIPTAN TABLETS. NARATRIPTAN tablets, for oral use
Initial U.S. Approval: 1998

1 INDICATIONS AND USAGE

Naratriptan Tablets are serotonin (5-HT1B/1D) receptor agonists (triptan) indicated for the acute treatment of migraine with or without aura in adults. (1)

Limitations of Use:

- Use only if a clear diagnosis of migraine has been established. (1)
- Not indicated for the prophylactic therapy of migraine attacks. (1)
- Not indicated for the treatment of cluster headache. (1)

2 DOSAGE AND ADMINISTRATION

- Recommended dose: 1 mg or 2.5 mg. (2.1)
- May repeat dose after 4 hours if needed; not to exceed 5 mg in any 24- hour period. (2.1)
- Mild or moderate renal or hepatic impairment: recommended starting dose is 1 mg not to exceed 2.5 mg in any 24-hour period. (2.2,2.3)

3 DOSAGE FORMS AND STRENGTHS

Tablets: 1 mg and 2.5 mg (3, 16)

4 CONTRAINDICATIONS

- History of coronary artery disease or coronary artery vasospasm (4)
- Wolff-Parkinson-White syndrome or other cardiac accessory conduction pathway disorders (4)
- History of stroke, transient ischemic attack, or hemiplegic or basilar migraine (4)
- Peripheral vascular disease (4)
- Ischemic bowel disease (4)
- Uncontrolled hypertension (4)
- Recent (within 24 hours) use of another 5-HT1 agonist (e.g., another triptan) or an ergotamine-containing medication (4)
- Hypersensitivity to naratriptan (angioedema and anaphylaxis seen) (4)
- Severe renal or hepatic impairment (4)

5 WARNINGS AND PRECAUTIONS

- Myocardial ischemia/infarction and Prinzmetal's angina: Perform cardiac evaluation in patients with multiple cardiovascular risk factors. (5.1)
- Arrhythmias: Discontinue naratriptan if occurs. (5.2)
- Chest/throat/neck/jaw pain, tightness, pressure, or heaviness: Generally not associated with myocardial ischemia; evaluate for CAD in patients at high risk. (5.3)
- Cerebral hemorrhage, subarachnoid hemorrhage, and stroke: Discontinue naratriptan if occurs. (5.4)
- Gastrointestinal ischemic reactions and peripheral vasospastic reactions: Discontinue naratriptan if occurs. (5.5)
- Medication overuse headache: Detoxification may be necessary. (5.6)
- Serotonin syndrome: Discontinue naratriptan if occurs. (5.7)

6 ADVERSE REACTIONS

Most common adverse reactions (≥2% and >placebo) were paresthesias, nausea, dizziness, drowsiness, malaise/fatigue, and throat/neck symptoms. (6.1)

To report SUSPECTED ADVERSE REACTIONS, contact Avet Pharmaceuticals Inc. at 1-866-901-DRUG (3784) or FDA at 1-800-FDA-1088 or www.fda.gov/medwatch.

8 USE IN SPECIFIC POPULATIONS

Pregnancy: Based on animal data, may cause fetal harm. (8.1)

FULL PRESCRIBING INFORMATION

1 INDICATIONS AND USAGE

Naratriptan tablets are indicated for the acute treatment of migraine with or without aura in adults.

Limitations of Use:

- Use only if a clear diagnosis of migraine has been established. If a patient has no response to the first migraine attack treated with naratriptan tablets reconsider the diagnosis of migraine before naratriptan tablets are administered to treat any subsequent attacks.
- Naratriptan tablets are not indicated for the prevention of migraine attacks.
- Safety and effectiveness of naratriptan tablets have not been established for cluster headache.

2 DOSAGE AND ADMINISTRATION

2.1 Dosing Information

The recommended dose of naratriptan tablets is 1 mg or 2.5 mg.

If the migraine returns or if the patient has only partial response, the dose may be repeated once after 4 hours, for a maximum dose of 5 mg in a 24-hour period.

The safety of treating an average of more than 4 migraine attacks in a 30-day period has not been established.

2.2 Dosage Adjustment in Patients With Renal Impairment

Naratriptan tablets are contraindicated in patients with severe renal impairment (creatinine clearance: <15 mL/min) because of decreased clearance of the drug [see Contraindications (4) , Use in Specific Populations (8.6) , Clinical Pharmacology (12.3) ].

In patients with mild to moderate renal impairment, the maximum daily dose should not exceed 2.5 mg over a 24-hour period and a 1-mg starting dose is recommended [see Use in Specific Populations (8.6) , Clinical Pharmacology (12.3) ].

2.3 Dosage Adjustment in Patients With Hepatic Impairment

Naratriptan tablets are contraindicated in patients with severe hepatic impairment (Child-Pugh Grade C) because of decreased clearance [see Contraindications (4) , Use in Specific Populations (8.7) , Clinical Pharmacology (12.3) ].

In patients with mild or moderate hepatic impairment (Child-Pugh Grade A or B), the maximum daily dose should not exceed 2.5 mg over a 24-hour period and a 1-mg starting dose is recommended [see Use in Specific Populations (8.7) , Clinical Pharmacology (12.3) ].

3 DOSAGE FORMS AND STRENGTHS

1-mg yellow, round, biconvex film-coated tablets, debossed with 'I53'

2.5-mg white, 'D' shaped, biconvex film-coated tablets, debossed with 'I54'

4 CONTRAINDICATIONS

Naratriptan tablets are contraindicated in patients with:

- Ischemic coronary artery disease (CAD) (angina pectoris, history of myocardial infarction, or documented silent ischemia) or coronary artery vasospasm, including Prinzmetal's angina [see Warnings and Precautions (5.1) ]
- Wolff-Parkinson-White syndrome or arrhythmias associated with other cardiac accessory conduction pathway disorders [see Warnings and Precautions (5.2) ]
- History of stroke or transient ischemic attack (TIA) or history of hemiplegic or basilar migraine because such patients are at a higher risk of stroke [see Warnings and Precautions (5.4) ]
- Peripheral vascular disease [see Warnings and Precautions (5.5) ]
- Ischemic bowel disease [see Warnings and Precautions (5.5) ]
- Uncontrolled hypertension [see Warnings and Precautions (5.8) ]
- Recent use (i.e., within 24 hours) of another 5-HT 1 agonist, ergotamine-containing medication, ergot-type medication (such as dihydroergotamine or methysergide) [see Drug Interactions (7.1, 7.2)]
- Hypersensitivity to naratriptan (angioedema and anaphylaxis seen) [see Warnings and Precautions (5.9)]
- Severe renal or hepatic impairment [see Use in Specific Populations (8.6, 8.7), Clinical Pharmacology (12.3)]

5 WARNINGS AND PRECAUTIONS

5.1 Myocardial Ischemia, Myocardial Infarction, and Prinzmetal's Angina

Naratriptan is contraindicated in patients with ischemic or vasospastic CAD. There have been rare reports of serious cardiac adverse reactions, including acute myocardial infarction, occurring within a few hours following administration of naratriptan. Some of these reactions occurred in patients without known CAD. Naratriptan may cause coronary artery vasospasm (Prinzmetal's angina), even in patients without a history of CAD.

Perform a cardiovascular evaluation in triptan-naive patients who have multiple cardiovascular risk factors (e.g., increased age, diabetes, hypertension, smoking, obesity, strong family history of CAD) prior to receiving naratriptan. If there is evidence of CAD or coronary artery vasospasm, naratriptan is contraindicated. For patients with multiple cardiovascular risk factors who have a negative cardiovascular evaluation, consider administering the first dose of naratriptan in a medically supervised setting and performing an electrocardiogram (ECG) immediately following administration of naratriptan. For such patients, consider periodic cardiovascular evaluation in intermittent long-term users of naratriptan.

5.2 Arrhythmias

Life-threatening disturbances of cardiac rhythm, including ventricular tachycardia and ventricular fibrillation leading to death, have been reported within a few hours following the administration of 5-HT1 agonists. Discontinue naratriptan if these disturbances occur. Naratriptan is contraindicated in patients with Wolff-Parkinson-White syndrome or arrhythmias associated with other cardiac accessory conduction pathway disorders.

5.3 Chest, Throat, Neck, and/or Jaw Pain/Tightness/Pressure

Sensations of tightness, pain, and pressure in the chest, throat, neck, and jaw commonly occur after treatment with naratriptan and are usually non-cardiac in origin. However, perform a cardiac evaluation if these patients are at high cardiac risk. 5-HT1 agonists, including naratriptan, are contraindicated in patients with CAD and those with Prinzmetal's variant angina.

5.4 Cerebrovascular Events

Cerebral hemorrhage, subarachnoid hemorrhage, and stroke have occurred in patients treated with 5-HT1 agonists, and some have resulted in fatalities. In a number of cases, it appears possible that the cerebrovascular events were primary, the 5-HT1 agonist having been administered in the incorrect belief that the symptoms experienced were a consequence of migraine when they were not. Also, patients with migraine may be at increased risk of certain cerebrovascular events (e.g., stroke, hemorrhage, TIA). Discontinue naratriptan if a cerebrovascular event occurs.

Before treating headaches in patients not previously diagnosed as migraineurs, and in migraineurs who present with symptoms atypical for migraine, exclude other potentially serious neurological conditions. Naratriptan is contraindicated in patients with a history of stroke or TIA.

5.5 Other Vasospasm Reactions

Naratriptan may cause non-coronary vasospastic reactions, such as peripheral vascular ischemia, gastrointestinal vascular ischemia and infarction (presenting with abdominal pain and bloody diarrhea), splenic infarction, and Raynaud's syndrome. In patients who experience symptoms or signs suggestive of non-coronary vasospasm reaction following the use of any 5-HT1 agonist, rule out a vasospastic reaction before receiving additional doses of naratriptan.

Reports of transient and permanent blindness and significant partial vision loss have been reported with the use of 5-HT1 agonists. Since visual disorders may be part of a migraine attack, a causal relationship between these events and the use of 5-HT1 agonists have not been clearly established.

5.6 Medication Overuse Headache

Overuse of acute migraine drugs (e.g., ergotamine, triptans, opioids, or combination of these drugs for 10 or more days per month) may lead to exacerbation of headache (medication overuse headache). Medication overuse headache may present as migraine-like daily headaches or as a marked increase in frequency of migraine attacks. Detoxification of patients, including withdrawal of the overused drugs, and treatment of withdrawal symptoms (which often includes a transient worsening of headache) may be necessary.

5.7 Serotonin Syndrome

Serotonin syndrome may occur with naratriptan, particularly during co-administration with selective serotonin reuptake inhibitors (SSRIs), serotonin norepinephrine reuptake inhibitors (SNRIs), tricyclic antidepressants (TCAs), and monoamine oxidase (MAO) inhibitors [see Drug Interactions (7.3)]. Serotonin syndrome symptoms may include mental status changes (e.g., agitation, hallucinations, coma), autonomic instability (e.g., tachycardia, labile blood pressure, hyperthermia), neuromuscular aberrations (e.g., hyperreflexia, incoordination), and/or gastrointestinal symptoms (e.g., nausea, vomiting, diarrhea). The onset of symptoms usually occurs within minutes to hours of receiving a new or a greater dose of a serotonergic medication. Discontinue naratriptan if serotonin syndrome is suspected.

5.8 Increase in Blood Pressure

Significant elevation in blood pressure, including hypertensive crisis with acute impairment of organ systems, has been reported on rare occasions in patients treated with 5-HT1 agonists, including patients without a history of hypertension. Monitor blood pressure in patients treated with naratriptan. Naratriptan is contraindicated in patients with uncontrolled hypertension.

5.9 Anaphylactic Reactions

There have been reports of anaphylaxis and hypersensitivity reactions, including angioedema, in patients receiving naratriptan. Such reactions can be life threatening or fatal. In general, anaphylactic reactions to drugs are more likely to occur in individuals with a history of sensitivity to multiple allergens. Naratriptan is contraindicated in patients with a history of hypersensitivity reaction to naratriptan.

6 ADVERSE REACTIONS

The following adverse reactions are discussed in more detail in other sections of the prescribing information:

- Myocardial ischemia, myocardial infarction, and Prinzmetal's angina [see Warnings and Precautions (5.1)]
- Arrhythmias [see Warnings and Precautions (5.2) ]
- Chest, throat, neck, and/or jaw pain/tightness/pressure [see Warnings and Precautions (5.3) ]
- Cerebrovascular events [see Warnings and Precautions (5.4) ]
- Other vasospasm reactions [seeWarnings and Precautions (5.5) ]
- Medication overuse headache [see Warnings and Precautions (5.6) ]
- Serotonin syndrome [see Warnings and Precautions (5.7) ]
- Increase in blood pressure [see Warnings and Precautions (5.8) ]
- Hypersensitivity reactions [see Contraindications (4) , Warnings and Precautions (5.9) ]

6.1 Clinical Trials Experience

Because clinical trials are conducted under widely varying conditions, adverse reaction rates observed in the clinical trials of a drug cannot be directly compared with rates in the clinical trials of another drug and may not reflect the rates observed in practice.

In a long-term open-label trial where patients were allowed to treat multiple migraine attacks for up to 1 year, 15 patients (3.6%) discontinued treatment due to adverse reactions.

In controlled clinical trials, the most common adverse reactions were paresthesias, dizziness, drowsiness, malaise/fatigue, and throat/neck symptoms, which occurred at a rate of 2% and at least 2 times placebo rate.

Table 1 lists the adverse reactions that occurred in 5 placebo-controlled clinical trials of approximately 1,752 exposures to placebo and naratriptan tablets in adult patients with migraine. Only reactions that occurred at a frequency of 2% or more in groups treated with naratriptan tablets 2.5 mg and that occurred at a frequency greater than the placebo group in the 5 pooled trials are included in Table 1.

Table 1. Adverse Reactions Reported by at Least 2% of Patients Treated With Naratriptan Tablets and at a Frequency Greater Than Placebo

Adverse Reaction | Percent of Patients Reporting
Adverse Reaction | Naratriptan Tablets 1 mg; (n = 627) | Naratriptan Tablets 2.5 mg; (n = 627) | Placebo; (n = 498)
Atypical sensation | 2 | 4 | 1
Paresthesias (all types) | 1 | 2 | <1
Gastrointestinal | 6 | 7 | 5
Nausea | 4 | 5 | 4
Neurological | 4 | 7 | 3
Dizziness | 1 | 2 | 1
Drowsiness | 1 | 2 | <1
Malaise/fatigue | 2 | 2 | 1
Pain and pressure sensation | 2 | 4 | 2
Throat/neck symptoms | 1 | 2 | 1

The incidence of adverse reactions in controlled clinical trials was not affected by age or weight of the patients, duration of headache prior to treatment, presence of aura, use of prophylactic medications, or tobacco use. There were insufficient data to assess the impact of race on the incidence of adverse reactions.

7 DRUG INTERACTIONS

7.1 Ergot-Containing Drugs

Ergot-containing drugs have been reported to cause prolonged vasospastic reactions. Because these effects may be additive, use of ergotamine-containing or ergot-type medications (like dihydroergotamine or methysergide) and naratriptan within 24 hours of each other is contraindicated.

7.2 Other 5-HT1 Agonists

Concomitant use of other 5-HT1B/1D agonists (including triptans) within 24 hours of treatment with naratriptan is contraindicated because the risk of vasospastic reactions may be additive.

7.3 Selective Serotonin Reuptake Inhibitors/Serotonin Norepinephrine Reuptake Inhibitors and Serotonin Syndrome

Cases of serotonin syndrome have been reported during co-administration of triptans and SSRIs, SNRIs, TCAs, and MAO inhibitors [see Warnings and Precautions (5.7) ].

8 USE IN SPECIFIC POPULATIONS

8.1 Pregnancy

Risk Summary

There are no adequate data on the developmental risk associated with use of naratriptan in pregnant women. Data from a prospective pregnancy exposure registry and epidemiological studies of pregnant women have documented outcomes in women exposed to naratriptan during pregnancy; however, due to small sample sizes, no definitive conclusions can be drawn regarding the risk of birth defects following exposure to naratriptan [ see Data ]. In animal studies, naratriptan produced developmental toxicity (including embryolethality and fetal abnormalities) when administered to pregnant rats and rabbits. The lowest doses producing evidence of developmental toxicity in animals were associated with plasma exposures 2.5 (rabbit) to 11 (rat) times that in humans at the maximum recommended daily dose (MRDD) [ see Data ].

In the U.S. general population, the estimated background risk of major birth defects and of miscarriage in clinically recognized pregnancies is 2% to 4% and 15% to 20%, respectively. The reported rate of major birth defects among deliveries to women with migraine ranged from 2.2% to 2.9% and of miscarriage was 17%, which were similar to rates reported in women without migraine.

Clinical Considerations

Disease-Associated Maternal and/or Embryo/Fetal Risk

Several studies have suggested that women with migraine may be at increased risk of preeclampsia during pregnancy.

Data

Human Data : The numbers of exposed pregnancy outcomes accumulated during the Sumatriptan/Naratriptan/ Treximet® (sumatriptan and naproxen sodium) Pregnancy Registry, a population-based international prospective study that collected data from October 1997 to September 2012, and smaller observational studies, were insufficient to define a level of risk for naratriptan in pregnant women. The Registry documented outcomes of 57 infants and fetuses exposed to naratriptan during pregnancy (52 exposed during the first trimester and 5 exposed during the second trimester). The occurrence of major birth defects (excluding fetal deaths and induced abortions without reported defects and all spontaneous pregnancy losses) during first-trimester exposure to naratriptan was 2.2% (1/46 [95% CI: 0.1% to 13.0%]) and during any trimester of exposure was 2.0% (1/51[95% CI: 0.1% to 11.8%]). Seven infants were exposed to both naratriptan and sumatriptan in utero, and one of these infants with first-trimester exposure was born with a major birth defect (ventricular septal defect). The sample size in this study had 80% power to detect at least a 3.8- to 4.6- fold increase in the rate of major malformations.

In a study using data from the Swedish Medical Birth Register, women who used triptans or ergots during pregnancy were compared with women who did not. Of the 22 births with first-trimester exposure to naratriptan, one infant was born with malformation (congenital deformity of the hand).

Animal Data : When naratriptan was administered to pregnant rats during the period of organogenesis at doses of 10, 60, or 340 mg/kg/day, there was a dose-related increase in embryonic death; incidences of fetal structural variations (incomplete/irregular ossification of skull bones, sternebrae, ribs) were increased at all doses. The maternal plasma exposures (AUC) at these doses were approximately 11, 70, and 470 times the exposure in humans at the MRDD. The high dose was maternally toxic, as evidenced by decreased maternal body weight gain during gestation. A no-effect dose for developmental toxicity in rats exposed during organogenesis was not established.

When naratriptan was administered orally (1, 5, or 30 mg/kg/day) to pregnant Dutch rabbits throughout organogenesis, the incidence of a specific fetal skeletal malformation (fused sternebrae) was increased at the high dose, the incidence of fetal variations (major blood vessel variations, supernumerary ribs, incomplete skeletal ossification) was increased at the mid and high doses, and embryonic death was increased at all doses (4, 20, and 120 times, respectively, the MRDD on a body surface area basis). Maternal toxicity (decreased body weight gain) was evident at the high dose. In a similar study in New Zealand White rabbits (1, 5, or 30 mg/kg/day throughout organogenesis), decreased fetal weights and increased incidences of fetal skeletal variations were observed at all doses (maternal exposures equivalent to 2.5, 19, and 140 times exposure in humans receiving the MRDD), while maternal body weight gain was reduced at 5 mg/kg or greater. A no-effect dose for developmental toxicity in rabbits exposed during organogenesis was not established.

When female rats were treated orally with naratriptan (10, 60, or 340 mg/kg/day) during late gestation and lactation, offspring behavioral impairment (tremors) and decreased offspring viability and growth were observed at doses of 60 mg/kg or greater, while maternal toxicity occurred only at the highest dose. Maternal exposures at the no-effect dose for developmental effects in this study were approximately 11 times the exposure in humans receiving the MRDD.

8.2 Lactation

Risk Summary

There are no data on the presence of naratriptan in human milk, the effects of naratriptan on the breastfed infant, or the effects of naratriptan on milk production. Naratriptan is present in rat milk.

The developmental and health benefits of breastfeeding should be considered along with the mother's clinical need for naratriptan and any potential adverse effects on the breastfed infant from naratriptan or from the underlying maternal condition.

8.4 Pediatric Use

Safety and effectiveness in pediatric patients have not been established. Therefore, naratriptan is not recommended for use in patients younger than18 years of age.

One controlled clinical trial evaluated naratriptan tablets (0.25 to 2.5 mg) in 300 adolescent migraineurs aged 12 to 17 years who received at least 1 dose of naratriptan tablets for an acute migraine. In this study, 54% of the patients were female and 89% were Caucasian. There were no statistically significant differences between any of the treatment groups. The headache response rates at 4 hours (n) were 65% (n = 74), 67% (n = 78), and 64% (n = 70) for placebo, 1-mg, and 2.5-mg groups, respectively. This trial did not establish the efficacy of naratriptan compared with placebo in the treatment of migraine in adolescents. Adverse reactions observed in this clinical trial were similar in nature to those reported in clinical trials in adults.

8.5 Geriatric Use

Clinical trials of naratriptan did not include sufficient numbers of patients aged 65 and older to determine whether they respond differently from younger patients. Other reported clinical experience has not identified differences in responses between the elderly and younger patients. In general, dose selection for an elderly patient should be cautious, usually starting at the low end of the dosing range, reflecting the greater frequency of decreased hepatic, renal, or cardiac function and of concomitant disease or other drug therapy.

Naratriptan is known to be substantially excreted by the kidney, and the risk of adverse reactions to this drug may be greater in elderly patients who have reduced renal function. In addition, elderly patients are more likely to have decreased hepatic function, they are at higher risk for CAD, and blood pressure increases may be more pronounced in the elderly.

A cardiovascular evaluation is recommended for geriatric patients who have other cardiovascular risk factors (e.g., diabetes, hypertension, smoking, obesity, strong family history of CAD) prior to receiving naratriptan [see Warnings and Precautions (5.1) ].

8.6 Renal Impairment

The use of naratriptan is contraindicated in patients with severe renal impairment (creatinine clearance: <15 mL/min) because of decreased clearance of the drug. In patients with mild to moderate renal impairment, the recommended starting dose is 1 mg, and the maximum daily dose should not exceed 2.5 mg over a 24-hour period [see Dosage and Administration (2.2), Clinical Pharmacology (12.3) ].

8.7 Hepatic Impairment

The use of naratriptan is contraindicated in patients with severe hepatic impairment (Child-Pugh Grade C) because of decreased clearance. In patients with mild or moderate hepatic impairment (Child-Pugh Grade A or B), the recommended starting dose is 1 mg, and the maximum daily dose should not exceed 2.5 mg over a 24-hour period [see Dosage and Administration (2.3), Clinical Pharmacology (12.3) ].

10 OVERDOSAGE

Adverse reactions observed after overdoses of up to 25 mg included increases in blood pressure resulting in lightheadedness, neck tension, tiredness, and loss of coordination. Also, ischemic ECG changes likely due to coronary artery vasospasm have been reported.

The elimination half-life of naratriptan is about 6 hours [see Clinical Pharmacology (12.3) ], and therefore monitoring of patients after overdose with naratriptan should continue for at least 24 hours or while symptoms or signs persist. There is no specific antidote to naratriptan. It is unknown what effect hemodialysis or peritoneal dialysis has on the serum concentrations of naratriptan.

11 DESCRIPTION

Naratriptan tablets, USP contains naratriptan hydrochloride, a selective 5-HT1B/1D receptor agonist. Naratriptan hydrochloride is chemically designated as N-methyl-3-(1-methyl-4-piperidinyl)-1H-indole-5-ethanesulfonamide monohydrochloride, and it has the following structure:

The empirical formula is C17 H25 N3 O2 S•HCl, representing a molecular weight of 371.93. Naratriptan hydrochloride is a white to pale yellow powder that is readily soluble in water.

Each naratriptan tablets, USP for oral administration contains 1.11 or 2.78 mg of naratriptan hydrochloride, equivalent to 1 or 2.5 mg of naratriptan, respectively. Each tablet also contains the inactive ingredients lactose anhydrous, microcrystalline cellulose, croscarmellose sodium, magnesium stearate. 1 mg tablet additionally contains opadry yellow, which contains: hypromellose 2910, titanium dioxide, polyethylene glycol 400 and iron oxide yellow. 2.5 mg tablet additionally contains opadry white, which contains: hypromellose 2910, talc, polyethylene glycol 8000 and titanium dioxide.

12 CLINICAL PHARMACOLOGY

12.1 Mechanism of Action

Naratriptan binds with high affinity to human cloned 5-HT1B/1D receptors. Migraines are likely due to local cranial vasodilatation and/or to the release of sensory neuropeptides (including substance P and calcitonin gene-related peptide) through nerve endings in the trigeminal system. The therapeutic activity of naratriptan for the treatment of migraine headache is thought to be due to the agonist effects at the 5-HT1B/1D receptors on intracranial blood vessels (including the arterio-venous anastomoses) and sensory nerves of the trigeminal system, which result in cranial vessel constriction and inhibition of pro-inflammatory neuropeptide release.

12.2 Pharmacodynamics

In the anesthetized dog, naratriptan has been shown to reduce the carotid arterial blood flow with little or no effect on arterial blood pressure or total peripheral resistance. While the effect on blood flow was selective for the carotid arterial bed, increases in vascular resistance of up to 30% were seen in the coronary arterial bed. Naratriptan has also been shown to inhibit trigeminal nerve activity in rat and cat.

In 10 subjects with suspected CAD undergoing coronary artery catheterization, there was a 1% to 10% reduction in coronary artery diameter following subcutaneous injection of 1.5 mg of naratriptan [see Contraindications (4) ].

12.3 Pharmacokinetics

Absorption: Naratriptan is well absorbed, with about 70% oral bioavailability. Following administration of a 2.5-mg tablet, the peak concentrations are obtained in 2 to 3 hours. After administration of 1-or 2.5-mg tablets, the Cmax is somewhat (about 50%) higher in women (not corrected for milligram-per-kilogram dose) than in men. During a migraine attack, absorption is slower, with a Tmax of 3 to 4 hours. Food does not affect the pharmacokinetics of naratriptan.

Naratriptan displays linear kinetics over the therapeutic dose range.

Distribution: The steady-state volume of distribution of naratriptan is 170 L. Plasma protein binding is 28% to 31% over the concentration range of 50 to 1,000 ng/mL.

Metabolism: In vitro, naratriptan is metabolized by a wide range of cytochrome P450 isoenzymes into a number of inactive metabolites.

Elimination: Naratriptan is predominantly eliminated in urine, with 50% of the dose recovered unchanged and 30% as metabolites in urine. The mean elimination half-life of naratriptan is 6 hours. The systemic clearance of naratriptan is 6.6 mL/min/kg. The renal clearance (220 mL/min) exceeds glomerular filtration rate, indicating active tubular secretion. Repeat administration of naratriptan tablets does not result in drug accumulation.

Special Populations:

Age: A small decrease in clearance (approximately 26%) was observed in healthy elderly subjects (65 to 77 years) compared with younger subjects, resulting in slightly higher exposure [see Use in Specific Populations (8.5) ].

Race: The effect of race on the pharmacokinetics of naratriptan has not been examined.

Renal Impairment: Clearance of naratriptan was reduced by 50% in subjects with moderate renal impairment (creatinine clearance: 18 to 39 mL/min) compared with the normal group. Decrease in clearances resulted in an increase of mean half-life from 6 hours (healthy) to 11 hours (range: 7 to 20 hours). The mean Cmax increased by approximately 40%. The effects of severe renal impairment (creatinine clearance: ≤ 15 mL/min) on the pharmacokinetics of naratriptan have not been assessed [see Contraindications (4) ].

Hepatic Impairment: Clearance of naratriptan was decreased by 30% in subjects with moderate hepatic impairment (Child-Pugh Grade A or B). This resulted in an approximately 40% increase in the half-life (range: 8 to 16 hours). The effects of severe hepatic impairment (Child-Pugh Grade C) on the pharmacokinetics of naratriptan have not been assessed [see Contraindications (4) ].

Drug Interaction Studies: From population pharmacokinetic analyses, co-administration of naratriptan and fluoxetine, beta-blockers, or tricyclic antidepressants did not affect the clearance of naratriptan.

Oral Contraceptives: Oral contraceptives reduced clearance by 32% and volume of distribution by 22%, resulting in slightly higher concentrations of naratriptan. Hormone replacement therapy had no effect on pharmacokinetics in older female patients.

Monoamine Oxidase and P450 Inhibitors: Naratriptan does not inhibit monoamine oxidase (MAO) enzymes and is a poor inhibitor of P450; metabolic interactions between naratriptan and drugs metabolized by P450 or MAO are therefore unlikely.

Smoking: Smoking increased the clearance of naratriptan by 30%.

Alcohol: In normal volunteers, co-administration of single doses of naratriptan tablets and alcohol did not result in substantial modification of naratriptan pharmacokinetic parameters.

13 NONCLINICAL TOXICOLOGY

13.1 Carcinogenesis, Mutagenesis, Impairment of Fertility

Carcinogenesis: In carcinogenicity studies, mice and rats were given naratriptan by oral gavage for 104 weeks. There was no evidence of an increase in tumors related to naratriptan administration in mice receiving up to 200 mg/kg/day. That dose was associated with a plasma (AUC) exposure that was 110 times the exposure in humans receiving the maximum recommended daily dose (MRDD) of 5 mg. Two rat studies were conducted, one using a standard diet and the other a nitrite-supplemented diet (naratriptan can be nitrosated in vitro to form a mutagenic product that has been detected in the stomachs of rats fed a high-nitrite diet). Doses of 5, 20, and 90 mg/kg were associated with AUC exposures that in the standard-diet study were 7, 40, and 236 times, respectively, and in the nitrite-supplemented-diet study were 7, 29, and 180 times, respectively, the exposure in humans at the MRDD. In both studies, there was an increase in the incidence of thyroid follicular hyperplasia in high-dose males and females and in thyroid follicular adenomas in high-dose males. In the standard-diet study only, there was also an increase in the incidence of benign c-cell adenomas in the thyroid of high-dose males and females. The exposures achieved at the no-effect dose for thyroid tumors were 40 (standard diet) and 29 (nitrite-supplemented diet) times the exposure achieved in humans at the MRDD. In the nitrite-supplemented diet study only, the incidence of benign lymphocytic thymoma was increased in all treated groups of females. It was not determined if the nitrosated product is systemically absorbed. However, no changes were seen in the stomachs of rats in that study.

Mutagenesis: Naratriptan was not mutagenic when tested in in vitro gene mutation (Ames and mouse lymphoma tk) assays. Naratriptan was also negative in the in vitro human lymphocyte assay and the in vivo mouse micronucleus assay. Naratriptan can be nitrosated in vitro to form a mutagenic product (WHO nitrosation assay) that has been detected in the stomachs of rats fed a nitrite-supplemented diet.

Impairment of Fertility: In a reproductive toxicity study in which male and female rats were administered naratriptan orally prior to and throughout the mating period (10, 60, 170, or 340 mg/kg/day; plasma exposures [AUC] approximately 11, 70, 230, and 470 times, respectively, the human exposure at the MRDD), there was a drug-related decrease in the number of females exhibiting normal estrous cycles at doses of 170 mg/kg/day or greater and an increase in preimplantation loss at 60 mg/kg/day or greater. In high-dose males, testicular/epididymal atrophy accompanied by spermatozoa depletion reduced mating success and may have contributed to the observed preimplantation loss. The exposures achieved at the no-effect doses for preimplantation loss, anestrus, and testicular effects were approximately 11, 70, and 230 times, respectively, the exposures in humans at the MRDD.

In a study in which rats were dosed orally with naratriptan (10, 60, or 340 mg/kg/day) for 6 months, changes in the female reproductive tract including atrophic or cystic ovaries and anestrus were seen at the high dose. The exposure at the no-effect dose of 60 mg/kg was approximately 85 times that in humans at the MRDD.

14 CLINICAL STUDIES

The efficacy of naratriptan in the acute treatment of migraine headaches was evaluated in 3 randomized, double-blind, placebo-controlled trials in adult patients (Trials 1, 2, 3). These trials enrolled adult patients who were predominantly female (86%) and Caucasian (96%) with a mean age of 41 years (range: 18 to 65 years). In all studies, patients were instructed to treat at least 1 moderate to severe headache. Headache response, defined as a reduction in headache severity from moderate or severe pain to mild or no pain, was assessed up to 4 hours after dosing. Associated symptoms such as nausea, vomiting, photophobia, and phonophobia were also assessed. Maintenance of response was assessed for up to 24 hours postdose. A second dose of naratriptan tablets or other rescue medication to treat migraines was allowed 4 to 24 hours after the initial treatment for recurrent headache.

In all 3 trials, the percentage of patients achieving headache response 4 hours after treatment, the primary outcome measure, was significantly greater among patients receiving naratriptan tablets compared with those who received placebo. In all trials, response to 2.5 mg was numerically greater than response to 1 mg and in the largest of the 3 trials, there was a statistically significant greater percentage of patients with headache response at 4 hours in the 2.5-mg group compared

Table 2. Percentage of Adult Patients With Headache Response (Mild or No Headache) 4 Hours Following Treatment
 | Naratriptan Tablets 1 mg (n =491) | Naratriptan Tablets 2.5 mg (n = 493) | Placebo (n = 395)
Trial 1 | 50%a | 60%a | 34%
Trial 2 | 52%a | 66%ab | 27%
Trial 3 | 54%a | 65%a | 32%
a P <0.05 compared with placebo.
b P <0.05 compared with 1 mg.

The estimated probability of achieving an initial headache response in adults over the 4 hours following treatment in pooled Trials 1, 2, and 3 is depicted in Figure 1.

Figure 1. Estimated Probability of Achieving Initial Headache Response Within 4 Hours in Pooled Trials 1, 2, and 3a

a The figure shows the probability over time of obtaining headache response (reduction in headache severity from moderate or severe pain to no or mild pain) following treatment with naratriptan tablets. In this Kaplan-Meier plot, patients not achieving response within 240 minutes were censored at 240 minutes.

For patients with migraine-associated nausea, photophobia, and phonophobia at baseline, there was a lower incidence of these symptoms 4 hours following administration of 1-mg and 2.5-mg naratriptan tablets compared with placebo.

Four to 24 hours following the initial dose of study treatment, patients were allowed to use additional treatment for pain relief in the form of a second dose of study treatment or other rescue medication. The estimated probability of patients taking a second dose or other rescue medication to treat migraine over the 24 hours following the initial dose of study treatment is summarized in Figure 2.

Figure 2. Estimated Probability of Patients Taking a Second Dose of Naratriptan Tablets or Other Medication to Treat Migraine Over the 24 Hours Following the Initial Dose of Study Treatment in Pooled Trials 1, 2 and 3 a

a Kaplan-Meier plot based on data obtained in the 3 controlled clinical trials (Trials 1, 2, and 3) providing evidence of efficacy with patients not using additional treatments censored at 24 hours.

The plot also includes patients who had no response to the initial dose. Remedication was discouraged prior to 4 hours postdose.

There is no evidence that doses of 5 mg provided a greater effect than 2.5 mg. There was no evidence to suggest that treatment with naratriptan was associated with an increase in the severity or frequency of migraine attacks. The efficacy of naratriptan was unaffected by presence of aura; gender, age, or weight of the subject; oral contraceptive use; or concomitant use of common migraine prophylactic drugs (e.g., beta-blockers, calcium channel blockers, tricyclic antidepressants). There was insufficient data to assess the impact of race on efficacy.

16 HOW SUPPLIED/STORAGE AND HANDLING

Naratriptan tablets, USP containing 1 mg and 2.5 mg of naratriptan (base) as the hydrochloride.

Naratriptan tablets, USP 1 mg, are yellow, round, biconvex film-coated tablets, debossed with 'I53' on one side and plain on the other side in blister packs of 9 tablets (NDC 23155-054-19), in HDPE container packs of 30 tablets (NDC 23155-054-03), and 500 tablets (23155-054-05).

Naratriptan tablets, USP 2.5 mg, are white, 'D' shaped, biconvex film-coated tablets, debossed with 'I54' on one side and plain on the other side in blister packs of 9 tablets (23155-055-19), in HDPE container packs of 30 tablets (NDC 23155-055-03), and 500 tablets (NDC 23155-055-05).

Store at 20º to 25ºC (68º to 77ºF). [See USP Controlled Room Temperature].

17 PATIENT COUNSELING INFORMATION

Advise the patient to read the FDA-approved patient labeling (Patient Information).

Risk of Myocardial Ischemia and/or Infarction, Prinzmetal's Angina, Other Vasospasm-Related Events, Arrhythmias, and Cerebrovascular Events: Inform patients that naratriptan tablets may cause serious cardiovascular side effects such as myocardial infarction or stroke. Although serious cardiovascular events can occur without warning symptoms, patients should be alert for the signs and symptoms of chest pain, shortness of breath, irregular heartbeat, significant rise in blood pressure, weakness, and slurring of speech and should ask for medical advice if any indicative sign or symptoms are observed. Apprise patients of the importance of this follow-up [see Warnings and Precautions (5.1, 5.2, 5.4, 5.5, 5.8)].

Anaphylactic Reactions: Inform patients that anaphylactic reactions have occurred in patients receiving naratriptan tablets. Such reactions can be life threatening or fatal. In general, anaphylactic reactions to drugs are more likely to occur in individuals with a history of sensitivity to multiple allergens [see Contraindications (4), Warnings and Precautions (5.9)].

Concomitant Use With Other Triptans or Ergot Medications: Inform patients that use of naratriptan tablets within 24 hours of another triptan or an ergot-type medication (including dihydroergotamine or methysergide) is contraindicated [see Contraindications (4), Drug Interactions (7.1, 7.2)].

Serotonin Syndrome: Caution patients about the risk of serotonin syndrome with the use of naratriptan tablets or other triptans, particularly during combined use with SSRIs, SNRIs, TCAs, and MAO inhibitors [see Warnings and Precautions (5.7), Drug Interactions (7.3)].

Medication Overuse Headache: Inform patients that use of acute migraine drugs for 10 or more days per month may lead to an exacerbation of headache and encourage patients to record headache frequency and drug use (e.g., by keeping a headache diary) [see Warnings and Precautions (5.6) ].

Pregnancy: Advise patients to notify their healthcare provider if they become pregnant during treatment or intend to become pregnant [see Use in Specific Populations (8.1) ].

Lactation: Advise patients to notify their healthcare provider if they are breastfeeding or plan to breastfeed [see Use in Specific Populations (8.2) ].

Ability to Perform Complex Tasks: Treatment with naratriptan tablets may cause somnolence and dizziness; instruct patients to evaluate their ability to perform complex tasks after administration of naratriptan tablets.

Dispense with Patient Information available at: www.avetpharma.com/product

Manufactured by:

USV Private Limited

Daman - 396210, India

Manufactured for:

Avet Pharmaceuticals Inc.

East Brunswick, NJ 08816

1.866.901. DRUG (3784)

Revised: 04/2023

Patient Information

Dispense with Patient Information available at: www.avetpharma.com/product
Patient Information
NARATRIPTAN TABLETS, USP
(NAR-a-TRIP-tan)
Read this Patient Information before you start taking naratriptan tablets and each time you get a refill. There may be new information. This information does not take the place of talking with your healthcare provider about your medical condition or treatment.
What is the most important information I should know about naratriptan tablets?
Naratriptan tablets can cause serious side effects, including:
Heart attack and other heart problems. Heart problems may lead to death.
Stop taking naratriptan tablets and get emergency medical help right away if you have any of the following symptoms of a heart attack:
• discomfort in the center of your chest that lasts for more than a few minutes, or that goes away and comes back
• severe tightness, pain, pressure, or heaviness in your chest, throat, neck, or jaw
• pain or discomfort in your arms, back, neck, jaw, or stomach
• shortness of breath with or without chest discomfort
• breaking out in a cold sweat
• nausea or vomiting
• feeling lightheaded
Naratriptan tablets are not for people with risk factors for heart disease unless a heart exam is done and shows no problem. You have a higher risk for heart disease if you:
• have high blood pressure
• have high cholesterol levels
• smoke
• are overweight
• have diabetes
• have a family history of heart disease
What are naratriptan tablets?
Naratriptan tablets are prescription medicine used to treat acute migraine headaches with or without aura in adults who have been diagnosed with migraine headaches.
Naratriptan tablets are not used to prevent or decrease the number of migraine headaches you have.
Naratriptan tablets are not used to treat other types of headaches such as hemiplegic migraines (that make you unable to move on one side of your body) or basilar migraines (rare form of migraine with aura).
It is not known if naratriptan tablets are safe and effective to treat cluster headaches.
It is not known if naratriptan tablets are safe and effective in children younger than 18 years of age.
Who should not take naratriptan tablets?
Do not take naratriptan tablets if you have:
• heart problems or a history of heart problems
• narrowing of blood vessels to your legs, arms, stomach, or kidney (peripheral vascular disease)
• uncontrolled high blood pressure
• severe kidney problems
• severe liver problems
• hemiplegic migraines or basilar migraines. If you are not sure if you have these types of migraines, ask your healthcare provider.
• had a stroke, transient ischemic attacks (TIAs), or problems with your blood circulation
• taken any of the following medicines in the last 24 hours:
• almotriptan (AXERT®)
• eletriptan (RELPAX®)
• frovatriptan (FROVA®)
• rizatriptan (MAXALT® , MAXALT-MLT®)
• sumatriptan (IMITREX® , SUMAVEL® DosePro® , ALSUMA®)
• sumatriptan and naproxen (TREXIMET®)
• ergotamines (CAFERGOT® , ERGOMAR® , MIGERGOT®)
• dihydroergotamine (D.H.E. 45® , MIGRANAL®)
Ask your healthcare provider if you are not sure if your medicine is listed above.
• an allergy to naratriptan or any of the ingredients in naratriptan tablets. See the end of this leaflet for a complete list of ingredients in naratriptan tablets.
What should I tell my healthcare provider before taking naratriptan tablets?
Before you take naratriptan tablets, tell your healthcare provider about all of your medical conditions, including if you:
• have high blood pressure
• have high cholesterol
• have diabetes
• smoke
• are overweight
• have heart problems or family history of heart problems or stroke
• have kidney problems
• have liver problems
• are not using effective birth control
• are pregnant or plan to become pregnant
• are breastfeeding or plan to breastfeed. It is not known if naratriptan tablets passes into your breast milk. Talk with your healthcare provider about the best way to feed your baby if you take naratriptan tablets.
Tell your healthcare provider about all the medicines you take, including prescription and over-the counter medicines, vitamins, and herbal supplements.
Using naratriptan tablets with certain other medicines can affect each other, causing serious side effects.
Especially tell your healthcare provider if you take anti-depressant medicines
called:
• selective serotonin reuptake inhibitors (SSRIs)
• serotonin norepinephrine reuptake inhibitors (SNRIs)
• tricyclic antidepressants (TCAs)
• monoamine oxidase inhibitors (MAOIs)
Ask your healthcare provider or pharmacist for a list of these medicines if you are not sure.
Know the medicines you take. Keep a list of them to show your healthcare provider or pharmacist when you get a new medicine.
How should I take naratriptan tablets?
• Certain people should take their first dose of naratriptan tablets in their healthcare provider's office or in another medical setting. Ask your healthcare provider if you should take your first dose in a medical setting.
• Take naratriptan tablets exactly as your healthcare provider tells you to take it.
• Your healthcare provider may change your dose. Do not change your dose without first talking with your healthcare provider.
• Take naratriptan tablets with water or other liquids.
• If you do not get any relief after your first naratriptan tablet, do not take a second tablet without first talking with your healthcare provider.
• If your headache comes back or you only get some relief from your headache, you can take a second tablet 4 hours after the first tablet.
• Do not take more than a total of 5 mg of naratriptan tablets in a 24-hour period.
• Some people who take too many naratriptan tablets may have worse headaches (medication overuse headache). If your headaches get worse, your healthcare provider may decide to stop your treatment with naratriptan tablets.
• If you take too much naratriptan tablets, call your healthcare provider or go to the nearest hospital emergency room right away.
• You should write down when you have headaches and when you take naratriptan tablets so you can talk with your healthcare provider about how naratriptan tablets is working for you.
What should I avoid while taking naratriptan tablets?
Naratriptan tablets can cause dizziness, weakness, or drowsiness. If you have these symptoms, do not drive a car, use machinery, or do anything where you need to be alert.
What are the possible side effects of naratriptan tablets?
Naratriptan tablets may cause serious side effects. See "What is the most important information I should know about naratriptan tablets?"
These serious side effects include:
• changes in color or sensation in your fingers and toes (Raynaud's syndrome)
• stomach and intestinal problems (gastrointestinal and colonic ischemic events). Symptoms of gastrointestinal and colonic ischemic events include:
• sudden or severe stomach pain
• stomach pain after meals
• weight loss
• nausea or vomiting
• constipation or diarrhea
• bloody diarrhea
• fever
• problems with blood circulation to your legs and feet (peripheral vascular ischemia). Symptoms of peripheral vascular ischemia include:
• cramping and pain in your legs or hips
• feeling of heaviness or tightness in your leg muscles
• burning or aching pain in your feet or toes while resting
• numbness, tingling, or weakness in your legs
• cold feeling or color changes in 1 or both legs or feet
• medication overuse headaches. Some people who use too many naratriptan tablets may have worse headaches (medication overuse headache). If your headaches get worse, your healthcare provider may decide to stop your treatment with naratriptan tablets.
• serotonin syndrome. Serotonin syndrome is a rare but serious problem that can happen in people using naratriptan tablets, especially if naratriptan tablets are used with anti-depressant medicines called SSRIs, SNRIs, TCAs, or MAOIs. Call your healthcare provider right away if you have any of the following symptoms of serotonin syndrome:
• mental changes such as seeing things that are not there (hallucinations), agitation, or coma
• fast heartbeat
• changes in blood pressure
• high body temperature
• tight muscles
• trouble walking
The most common side effects of naratriptan tablets include:
• tingling or numbness in your fingers or toes
• dizziness
• warm, hot, burning feeling to your face (flushing)
• discomfort or stiffness in your neck
• feeling weak, drowsy, or tired
Tell your healthcare provider if you have any side effect that bothers you or that does not go away.
These are not all the possible side effects of naratriptan tablets. For more information, ask your healthcare provider or pharmacist.
Call your doctor for medical advice about side effects. You may report side effects to Avet Pharmaceuticals Inc. at 1-866-901-DRUG (3784) or FDA at 1-800-FDA-1088.
How should I store naratriptan tablets?
Store naratriptan tablets between 20°C and 25°C (68°F and 77°F). [See USP Controlled Room Temperature]
Keep naratriptan tablets and all medicines out of the reach of children.
General information about the safe and effective use of naratriptan tablets.
Medicines are sometimes prescribed for purposes other than those listed in Patient Information leaflets. Do not use naratriptan tablets for a condition for which it was not prescribed. Do not give naratriptan tablets to other people, even if they have the same symptoms you have. It may harm them.
This Patient Information leaflet summarizes the most important information about naratriptan tablets. If you would like more information, talk with your healthcare provider. You can ask your healthcare provider or pharmacist for information about naratriptan tablets that is written for healthcare professionals.
For more information, call 1-866-901-DRUG (3784).
What are the ingredients in naratriptan tablets?
Active ingredient: naratriptan hydrochloride
Inactive ingredients: lactose anhydrous, microcrystalline cellulose, croscarmellose sodium, magnesium stearate.
1 mg tablet additionally contains opadry yellow, which contains: hypromellose 2910, titanium dioxide, polyethylene glycol 400 and iron oxide yellow.
2.5 mg tablet additionally contains opadry white, which contains: hypromellose 2910, talc, polyethylene glycol 8000 and titanium dioxide.
This Patient Information has been approved by the U.S. Food and Drug Administration.
The brands listed are registered trademarks of their respective owners.
Dispense with Patient Information available at: www.avetpharma.com/product
Manufactured by:
USV Private Limited
Daman - 396210, India
Manufactured for:
Avet Pharmaceuticals Inc.
East Brunswick, NJ 08816
1.866.901.DRUG (3784)

Revised: 04/2023

PACKAGE LABEL.PRINCIPAL DISPLAY PANEL

Naratriptan Tablets, USP 1 mg, 9 Unit-of-Use Tablets

Naratriptan Tablets, USP 2.5 mg, 9 Unit-of-Use Tablets